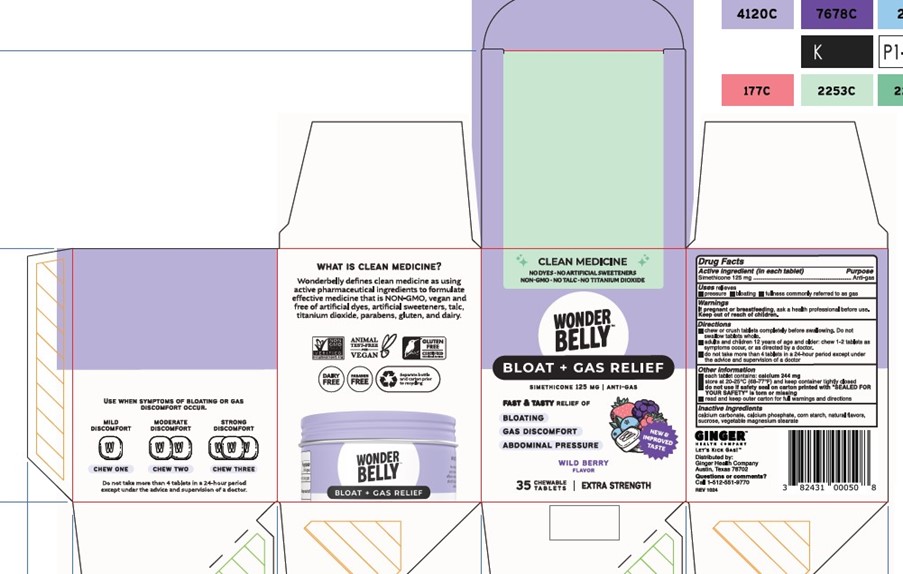 DRUG LABEL: Wonderbelly Extra Strength Anti-Gas
NDC: 82431-203 | Form: TABLET, CHEWABLE
Manufacturer: Ginger Health Company
Category: otc | Type: HUMAN OTC DRUG LABEL
Date: 20250630

ACTIVE INGREDIENTS: DIMETHICONE 125 mg/1 1
INACTIVE INGREDIENTS: CALCIUM CARBONATE; DIBASIC CALCIUM PHOSPHATE DIHYDRATE; MAGNESIUM STEARATE; SUCROSE; STARCH, CORN; TRIBASIC CALCIUM PHOSPHATE

Wild Berry Bloat + Gas

Drug Facts

Active ingredient (in each tablet)

Simethicone 125 mg

Purpose

Anti-gas

Uses

relieves

- pressure
- bloating
- fullness commonly referred to as gas

Warnings

PREGNANCY OR BREAST FEEDING

If pregnant or breastfeeding, ask a health professional before use

Keep out of reach of children.

Directions

- chew or crush tablets completely before swallowing. Do not swallow tablets whole.
- adults and children 12 years of age or older: chew 1-2 tablets as symptoms occur, or as directed by a doctor
- do not take more than 4 tablets in a 24-hour period except under the advice and supervision of a doctor

Other information

- each tablet contains: calcium 244 mg
- store at 20-25°C (68-77°F) and keep container tightly closed
- do not use if safety seal on carton printed with "SEALED FOR YOUR SAFETY" is torn or missing
- read and keep outer carton for full warnings and directions

Inactive ingredients

calcium carbonate, calcium phosphate, corn starch, natural flavors, sucrose, vegetable magnesium stearate

Questions or comments?

Call 1-512-551-9770

Distributed by:

Ginger Health Company

Austin, Texas 78702

Principal Display Panel

CLEAN MEDICINE

No Dyes, No Artificial Sweeteners, Non-GMO, No Talc, No Titanium Dioxide

WONDERBELLY

BLOAT + GAS RELIEF

Simethicone 125 mg | Anti-gas

Fast and Tasty Relief of

Bloating

Gas Discomfort

Abdominal Pressure

WILD BERRY

Flavor

35 Chewable Tablets | Extra Strength